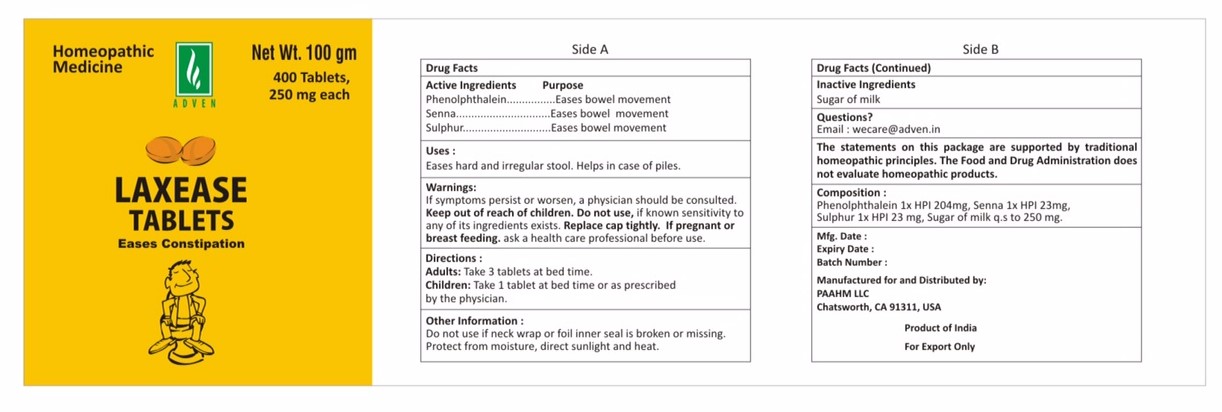 DRUG LABEL: laxease
NDC: 69825-006 | Form: TABLET
Manufacturer: Adven Biotech Private Limited
Category: homeopathic | Type: HUMAN OTC DRUG LABEL
Date: 20160330

ACTIVE INGREDIENTS: PHENOLPHTHALEIN 81.6 g/100 g; SENNA LEAF 9.2 g/100 g; SULFUR 9.2 g/100 g
INACTIVE INGREDIENTS: LACTOSE

Laxease Tablets

ACTIVE INGREDIENT

Phenolphthalein, Senna, Sulphur

DOSAGE AND ADMINISTRATION

Adults: Take 3 tablets at bed time.

Children under 18 years: Take 1 tablets at bed time or as prescribed by the physician.

WARNINGS

If symptons persist or worsen, a physician should be consulted. Keep out of reach of children. Do not use, if known sentivity to any of its ingredients exists. Replace cap tightly. If pregnant or breast feeding, ask a health care professional before use.

PURPOSE

Eases hard and irregular stool. Helps in case of piles.

INDICATIONS AND USAGE

Eases bowel movement.

INACTIVE INGREDIENT

Sugar of milk

Do not use if neck wrap or foil inner seal is broken or missing. Protect from moisture, direct sunlight and heat.